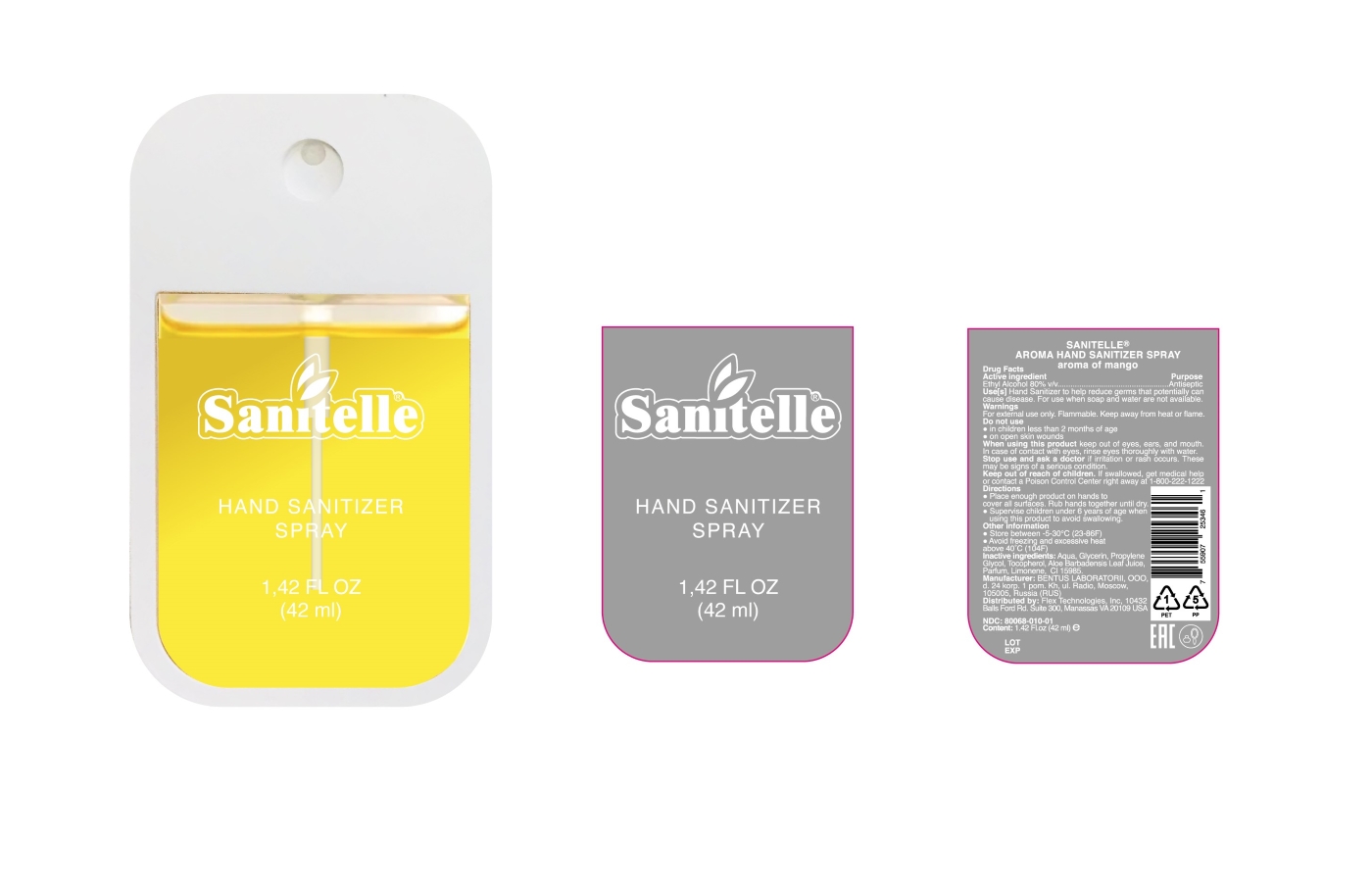 DRUG LABEL: Sanitelle Hand Sanitizer Aroma Mango
NDC: 80068-010 | Form: SPRAY
Manufacturer: BENTUS LABORATORII, OOO
Category: otc | Type: HUMAN OTC DRUG LABEL
Date: 20210427

ACTIVE INGREDIENTS: ALCOHOL 80 mL/100 mL
INACTIVE INGREDIENTS: FD&C YELLOW NO. 6; GLYCERIN 1.45 mL/100 mL; WATER; PROPYLENE GLYCOL; TOCOPHEROL; ALOE VERA LEAF; LIMONENE, (+)-

Active Ingredient(s)

Alcohol 80% v/v. Purpose: Antiseptic

Purpose

Antiseptic, Hand Sanitizer

Use

Hand Sanitizer to help reduce bacteria that potentially can cause disease. For use when soap and water are not available.

Warnings

For external use only. Flammable. Keep away from heat or flame

Do not use

- in children less than 2 months of age
- on open skin wounds

When using this product keep out of eyes, ears, and mouth. In case of contact with eyes, rinse eyes thoroughly with water.
Stop use and ask a doctor if irritation or rash occurs. These may be signs of a serious condition.
Keep out of reach of children. If swallowed, get medical help or contact a Poison Control Center right away.

Stop use and ask a doctor if irritation or rash occurs. These may be signs of a serious condition.

Keep out of reach of children. If swallowed, get medical help or contact a Poison Control Center right away.

Directions

- Place enough product on hands to cover all surfaces. Rub hands together until dry.
- Supervise children under 6 years of age when using this product to avoid swallowing.

Other information

- Store between 15-30C (59-86F)
- Avoid freezing and excessive heat above 40C (104F)

Inactive ingredients

Aqua, Glycerin, Propylene Glycol, Tocopherol, Aloe Barbadensis Leaf Juice, Parfum, Limonene, CI 15985

Package Label - Principal Display Panel

Distributed by: Flex Technologies, Inc, 10432 Balls Ford Rd. Suite 300, Manassas, VA 20109, USA